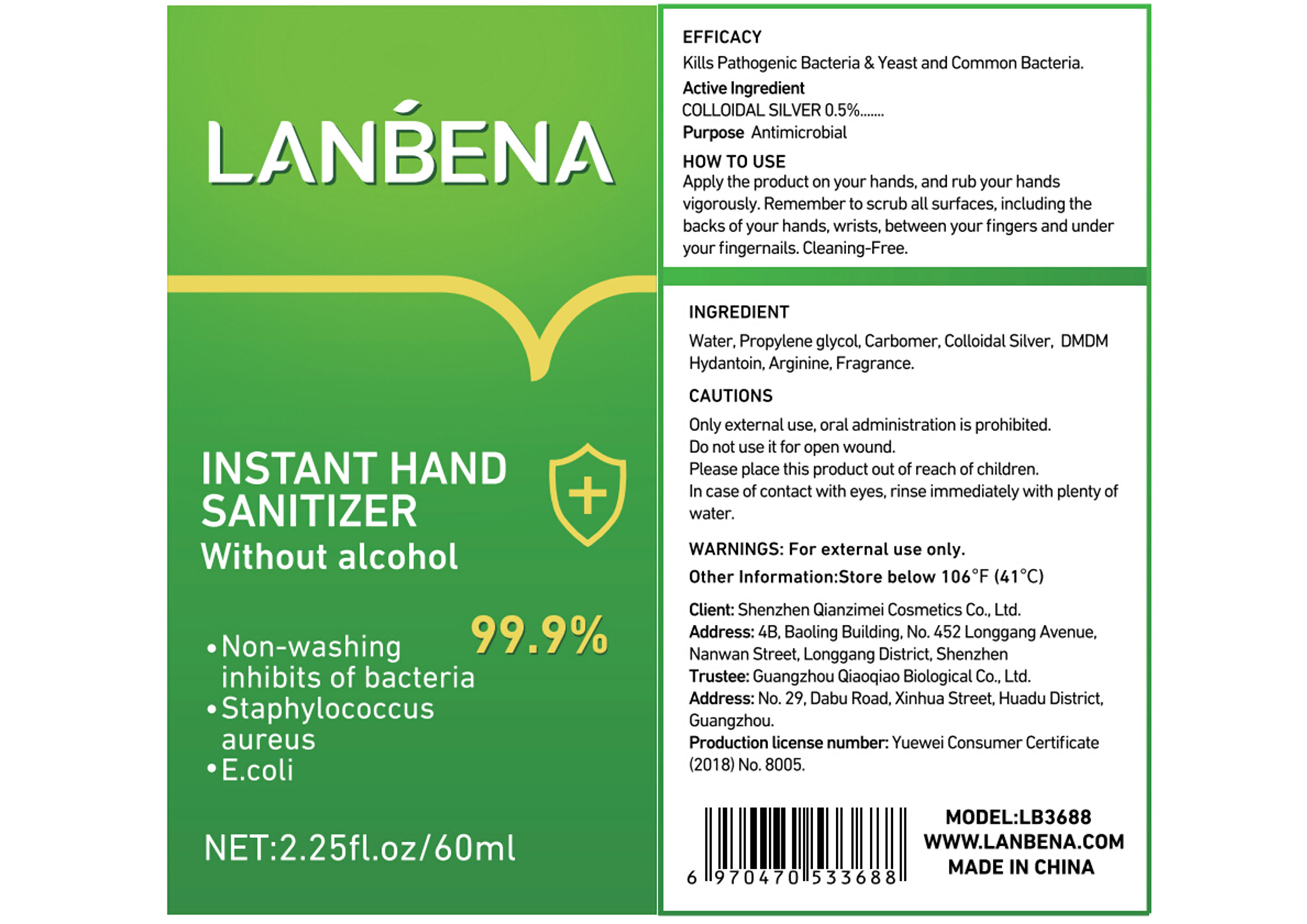 DRUG LABEL: INSTANT HAND SANITIZER
NDC: 75000-001 | Form: GEL
Manufacturer: Shenzhen Qianzimei Cosmetics Co., Ltd.
Category: otc | Type: HUMAN OTC DRUG LABEL
Date: 20200914

ACTIVE INGREDIENTS: SILVER 0.5 g/100 mL
INACTIVE INGREDIENTS: ARGININE; WATER; PROPYLENE GLYCOL; CARBOMER HOMOPOLYMER, UNSPECIFIED TYPE; DMDM HYDANTOIN

75000-001
INSTANT HAND SANITIZER

Active Ingredient

COLLOIDAL SILVER 0.5%

Purpose

Antimicrobial

Uses

Apply the product on your hands,and rub your hands vigorously.Remember to scrub all surfaces, including the

backs of your hands,wrists, between your fingers and under your fingernails.Cleaning-Free.

WARNINGS

For external use only.

Other Information

Store below 106°F(41°C)

Inactive ingredients

Water, ROPYLENE GLYCOL, Carbomer,DMDM Hydantoin,Arginine,Fragrance.